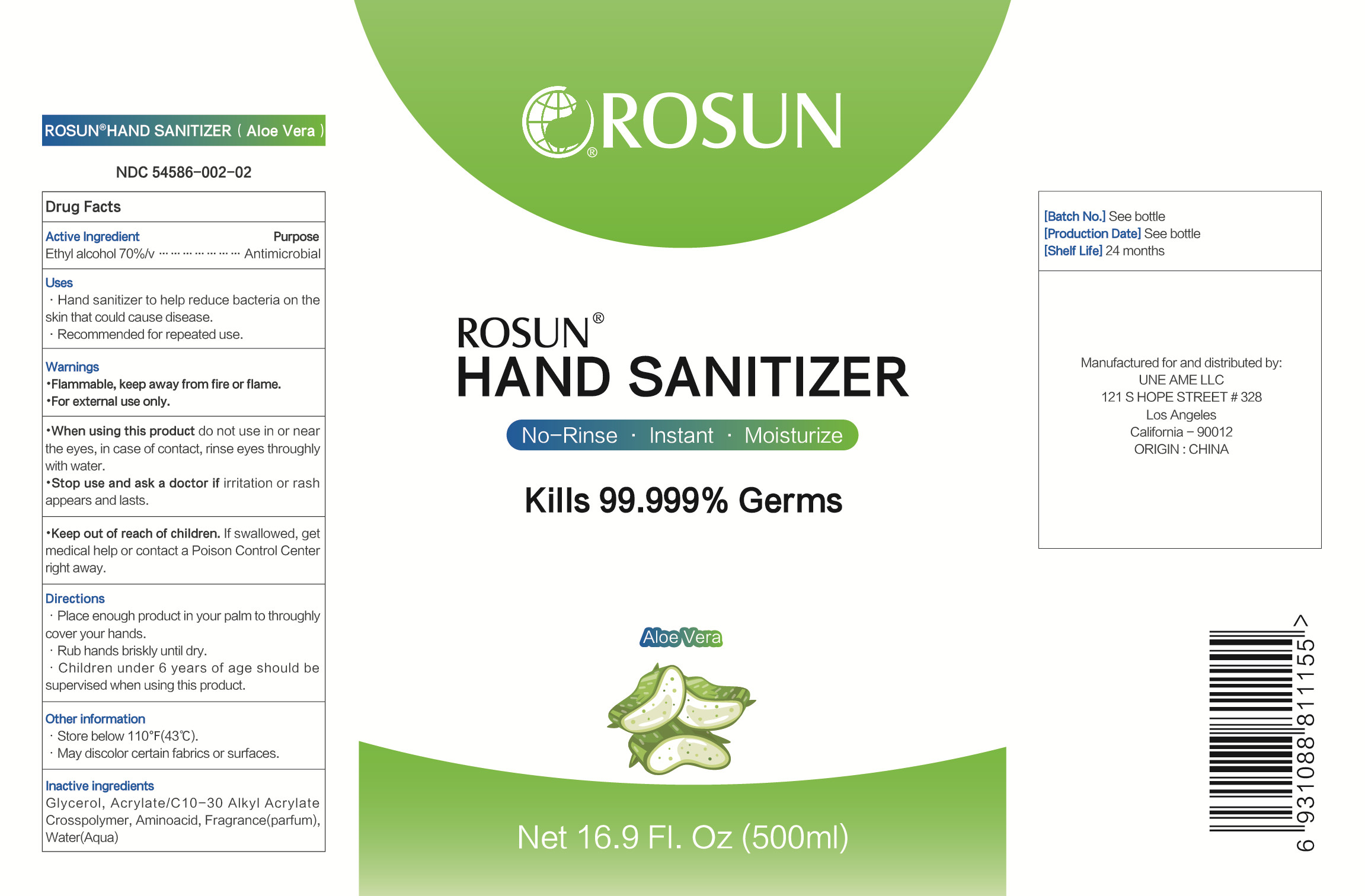 DRUG LABEL: Hand Sanitizer
NDC: 54586-002 | Form: GEL
Manufacturer: Chengdu Rosun Disinfection Pharmaceutical Co., Ltd.
Category: otc | Type: HUMAN OTC DRUG LABEL
Date: 20200804

ACTIVE INGREDIENTS: ALCOHOL 375 mL/500 mL
INACTIVE INGREDIENTS: GLYCERIN; AMINO ACIDS, ESSENTIAL; CARBOMER INTERPOLYMER TYPE A (ALLYL SUCROSE CROSSLINKED); WATER

DOSAGE AND ADMINISTRATION

Store below 110°F(43°C).

INACTIVE INGREDIENT

Acrylate / C10-30 Alkyl Acrylate Crosspolymer

Glycerol

Amino acid

Purified Water

INDICATIONS AND USAGE

1.Place enough product in your palm to throughly cover your hands.
2.Rub hands briskly until dry.
3.Children under 6 years of age should be supervised when using this product.

ACTIVE INGREDIENT

Ethyl Alcohol

keep out of reach of children

PURPOSE

Disinfection
Sterilization
No Rinseing

WARNINGS

Flammable, keep away from fire or flame.For external use only.